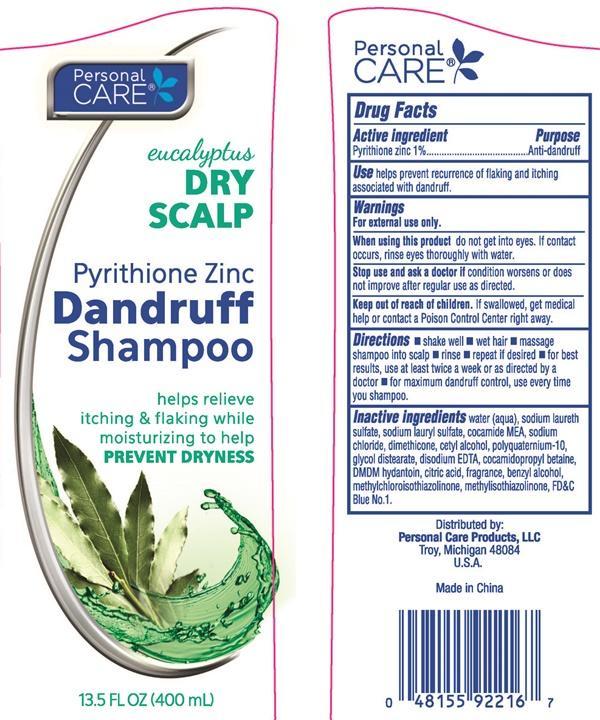 DRUG LABEL: Personal Care Pyrithione Zinc Dandruff
                        
                        
NDC: 29500-2216 | Form: SHAMPOO
Manufacturer: Personal Care Products, LLC
Category: otc | Type: HUMAN OTC DRUG LABEL
Date: 20160629

ACTIVE INGREDIENTS: PYRITHIONE ZINC 4.04 g/400 mL
INACTIVE INGREDIENTS: WATER; SODIUM LAURETH SULFATE; SODIUM LAURYL SULFATE; COCO MONOETHANOLAMIDE; SODIUM CHLORIDE; DIMETHICONE; CETYL ALCOHOL; POLYQUATERNIUM-10 (400 CPS AT 2%); GLYCOL DISTEARATE; EDETATE DISODIUM; COCAMIDOPROPYL BETAINE; DMDM HYDANTOIN; CITRIC ACID MONOHYDRATE; BENZYL ALCOHOL; METHYLCHLOROISOTHIAZOLINONE; METHYLISOTHIAZOLINONE; FD&C BLUE NO. 1

Personal Care Pyrithione Zinc Dandruff Shampoo - Dry Scalp Care

Drug Facts Active ingredient

Pyrithione Zinc 1%

Purpose

Anti-dandruff

Use

helps prevent recurrence of flaking and itching associated with dandruff.

Warning

For external use only.

When using this product

do not get into eyes. If contact occurs, rinse eyes thoroughly with water.

Stop use and ask a doctor if

condition worsens or does not improve after regular use as directed.

Keep out of reach of children.

If swallowed, get medical help or contact a Poison Control Center right away.

Directions

- shake well

- wet hair

- massage shampoo into scalp

- rinse

- repeat if desired

- for best results, use at least twice a week or as directed by a doctor

- for maximum dandruff control, use every time you shampoo.

Inactive Ingredients

water (aqua), sodium laureth sulfate, sodium lauryl sulfate, cocamide MEA, sodium chloride, dimethicone, cetyl alcohol, polyquaternium-10, glycol distearate, disodium EDTA, cocamidopropyl betain, DMDM hydantoin, citric acid, fragrance, benzyl alcohol, methylchloroisothiazolinone, methylisothiazolinone, FD and C Blue 1

Personal Care Dry Scalp Dandruff Shampoo

Personal Care

eucalyptus

DRY SCALP

Pyrithione Zinc

Dandruff

Shampoo

helps relieve itching & flaking while moisturizing to help

PREVENT DRYNESS

13.5 FL OZ (400 mL)

Distributed by:

Personal Care Products, LLC

Troy, Michigan 48084

U.S.A.

Made in China